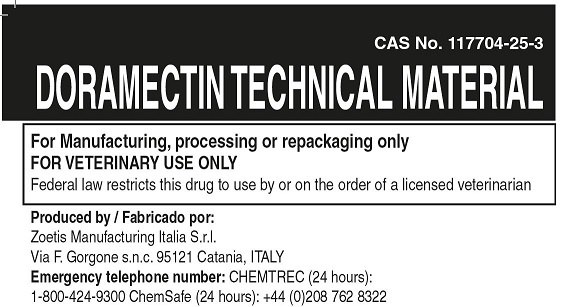 DRUG LABEL: Doramectin
NDC: 54771-0207 | Form: POWDER
Manufacturer: Zoetis Inc.
Category: other | Type: BULK INGREDIENT
Date: 20250808

ACTIVE INGREDIENTS: DORAMECTIN 1 kg/1 kg

Doramectin